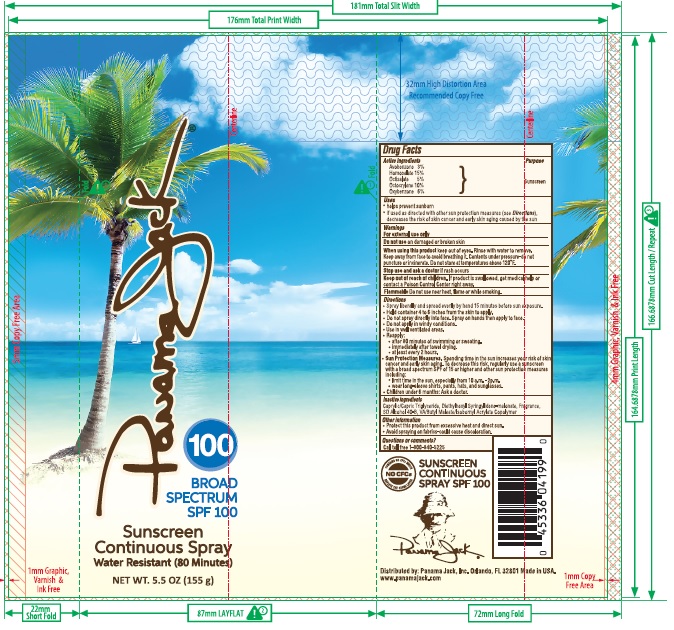 DRUG LABEL: Panama Jack
NDC: 13630-0124 | Form: SPRAY
Manufacturer: Prime Packaging Inc.
Category: otc | Type: HUMAN OTC DRUG LABEL
Date: 20200117

ACTIVE INGREDIENTS: AVOBENZONE 26.28 mg/1 mL; HOMOSALATE 131.4 mg/1 mL; OCTISALATE 43.8 mg/1 mL; OCTOCRYLENE 87.6 mg/1 mL; OXYBENZONE 52.56 mg/1 mL
INACTIVE INGREDIENTS: DIETHYLHEXYL SYRINGYLIDENEMALONATE; MEDIUM-CHAIN TRIGLYCERIDES; ALCOHOL; VINYL ACETATE; MONOBUTYL MALEATE; ISOBORNYL ACRYLATE

Panama Jack 100 Broad Spectrum SPF 100 Sunscreen Continuous Spray

Active Ingredients

Avobenzone 3%

Homosalate 15%

Octisalate 5%

Octocrylene 10%

Oxybenzone 6%

Purpose

Sunscreen

Uses

- helps prevent sunburn
- if used as directed with other sun protection measures (see Directions), decreases the risk of skin cancer and early skin aging caused by the sun

Warnings

For external use only

Do not use on damaged or broken skin

When using this product keep out of eyes. Risne with water to remove.

Keep away from face to avoid breathing it. Contents under pressure-do not puncture or incinerate. Do not store at temperatures above 120ºF.

Stop use and ask a doctor if rash occurs

Keep out of reach of children. If product is swallowed, get medical help or contact a Poison Control Center right away.

Flammable Do not use near heat, flame or while smoking.

Directions

- Spray liberally and spread evenly by hand 15 minutes before sun exposure.
- Hold container 4 to 6 inches from the skin to apply.
- Do not spray directly into face. Spray on hands then apply to face.
- Do not apply in windy conditions.
- Use in well ventilated areas.
- Reapply:
- after 80 minutes of swimming and sweating.
- immediately after towel drying.
- at least every 2 hours.
- Sun Protection Measures. Spending time in the sun increases your risk of skin cancer and early skin aging. To decrease this risk, regularly use a sunscreen with a broad spectrum SPF of 15 or higher and other sun protection measures including:
- limit time in the sun, especially from 10 a.m. - 2 p.m.
- wear long-sleeve shirts, pants, hats, and sunglasses.
- Children under 6 months: Ask a doctor.

Inactive Ingredients

Caprylic/Capric Triglyceride, Diethylhexyl Syringylidene-malonate, Fragrance, SD Alcohol 40-B, VA/Butyl Maleate/Isobornyl Acrylate Copolymer

Other Information

- Protect this product from excessive heat and direct sun.
- Avoid spraying on fabrics-could cause discoloration.

Question or comments?

Call toll free 1-800-840-5225